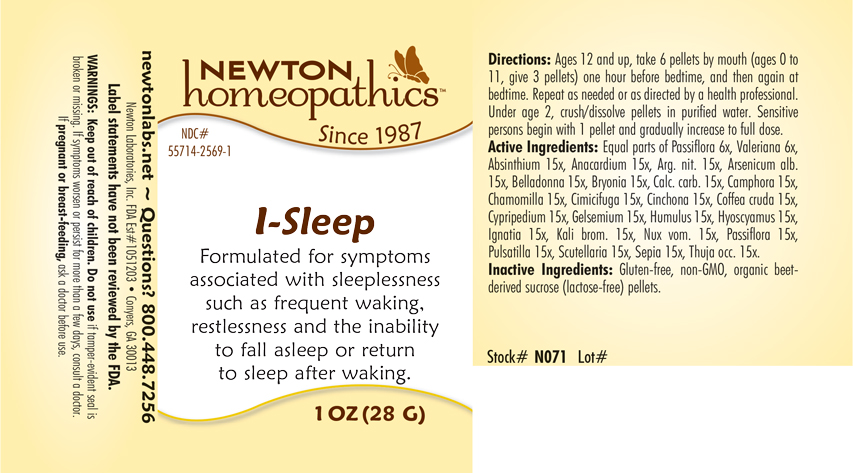 DRUG LABEL: I-Sleep
NDC: 55714-2569 | Form: PELLET
Manufacturer: Newton Laboratories, Inc.
Category: homeopathic | Type: HUMAN OTC DRUG LABEL
Date: 20210201

ACTIVE INGREDIENTS: WORMWOOD 15 [hp_X]/1 g; SEMECARPUS ANACARDIUM JUICE 15 [hp_X]/1 g; SILVER NITRATE 15 [hp_X]/1 g; ARSENIC TRIOXIDE 15 [hp_X]/1 g; ATROPA BELLADONNA 15 [hp_X]/1 g; MATRICARIA CHAMOMILLA 15 [hp_X]/1 g; BRYONIA ALBA ROOT 15 [hp_X]/1 g; OYSTER SHELL CALCIUM CARBONATE, CRUDE 15 [hp_X]/1 g; CAMPHOR (NATURAL) 15 [hp_X]/1 g; BLACK COHOSH 15 [hp_X]/1 g; CINCHONA OFFICINALIS BARK 15 [hp_X]/1 g; ARABICA COFFEE BEAN 15 [hp_X]/1 g; CYPRIPEDIUM PARVIFLORUM VAR. PUBESCENS ROOT 15 [hp_X]/1 g; GELSEMIUM SEMPERVIRENS ROOT 15 [hp_X]/1 g; HOPS 15 [hp_X]/1 g; HYOSCYAMUS NIGER 15 [hp_X]/1 g; STRYCHNOS IGNATII SEED 15 [hp_X]/1 g; POTASSIUM BROMIDE 15 [hp_X]/1 g; STRYCHNOS NUX-VOMICA SEED 15 [hp_X]/1 g; SEPIA OFFICINALIS JUICE 15 [hp_X]/1 g; PASSIFLORA INCARNATA FLOWERING TOP 15 [hp_X]/1 g; ANEMONE PULSATILLA 15 [hp_X]/1 g; SCUTELLARIA LATERIFLORA WHOLE 15 [hp_X]/1 g; THUJA OCCIDENTALIS LEAFY TWIG 15 [hp_X]/1 g; VALERIAN 6 [hp_X]/1 g
INACTIVE INGREDIENTS: SUCROSE

I-Sleep 2569P

INDICATIONS & USAGE SECTION

Formulated for symptoms associated with sleeplessness such as frequent waking, restlessness and the inability to fall asleep or return to sleep after waking.

DOSAGE & ADMINISTRATION SECTION

Directions: Ages 12 and up, take 6 pellets by mouth (ages 0 to 11, give 3 pellets) one hour before bedtime, and then again at bedtime. Repeat as needed or as directed by a health professional. Under age 2, crush/dissolve pellets in purified water. Sensitive persons begin with 1 pellet and gradually increase to full dose.

OTC - ACTIVE INGREDIENT SECTION

Equal parts of Passiflora incarnata 6x, Valeriana officinalis 6x, Absinthium 15x, Anacardium orientale 15x, Argentum nitricum 15x, Arsenicum album 15x, Belladonna 15x, Bryonia 15x, Calcarea carbonica 15x, Camphora 15x, Chamomilla 15x, Cimicifuga racemosa 15x, Cinchona officinalis 15x, Coffea cruda 15x, Cypripedium pubescens 15x, Gelsemium sempervirens 15x, Humulus lupulus 15x, Hyoscyamus niger 15x, Ignatia amara 15x, Kali bromatum 15x, Nux vomica 15x, Passiflora incarnata 15x, Pulsatilla 15x, Scutellaria lateriflora 15x, Sepia 15x, Thuja occidentalis 15x.

OTC - PURPOSE SECTION

Formulated for symptoms associated with sleeplessness such as frequent waking, restlessness and the inability to fall asleep or return to sleep after after waking.

INACTIVE INGREDIENT SECTION

Inactive Ingredients: Gluten-free, non-GMO, organic beet-derived sucrose (lactose-free) pellets.

QUESTIONS SECTION

newtonlabs.net - Questions? 800.448.7256

Newton Laboratories, Inc. FDA Est # 1051203 - Conyers, GA 30013

WARNINGS SECTION

WARNINGS: Keep out of reach of children. Do not use if tamper-evident seal is broken or missing. If symptoms worsen or persist for more than a few days, consult a doctor. If pregnant or breast-feeding, ask a doctor before use.

OTC - PREGNANCY OR BREAST FEEDING SECTION

If pregnant or breast-feeding, ask a doctor before use.

OTC - KEEP OUT OF REACH OF CHILDREN SECTION

Keep out of reach of children.